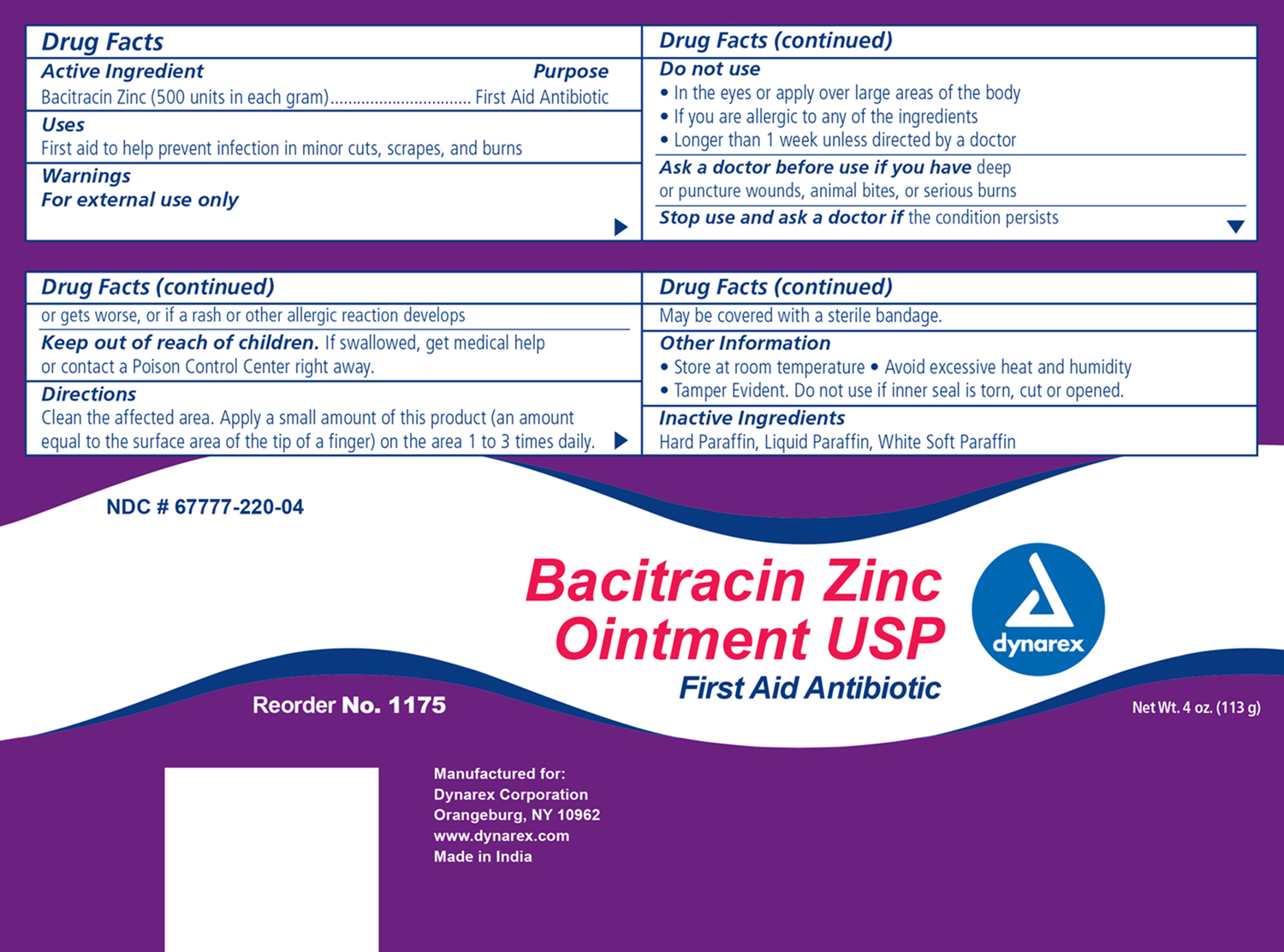 DRUG LABEL: Bacitracin Zinc
NDC: 67777-220 | Form: OINTMENT
Manufacturer: Dynarex Corporation
Category: otc | Type: HUMAN OTC DRUG LABEL
Date: 20170615

ACTIVE INGREDIENTS: BACITRACIN ZINC 500 [USP'U]/1 g
INACTIVE INGREDIENTS: PETROLATUM; LIGHT MINERAL OIL; MINERAL OIL

Bacitracin Zinc Ointment

Active ingredient Purpose
Bacitracin Zinc (500 Units in each gram) First Aid Antibiotic

Warnings:

For external use only

DOSAGE & ADMINISTRATION:

- clean the affected areas, Apply a small amount of product (an amount equal to the surface area of the tip of the finger) on the area 1 to 3 times daily. May be covered with a sterile bandage

Stop use and ask a doctor if the condition persists or gets worse, or if a rash or other allergic reaction develops.

Indications & Usage:

- in the eyes or over large areas of the body
- if you are allergic to any of the ingredients
- longer than 1 week unless directed by a doctor

Keep out of reach of children

If swallowed, get medical help or contact a Poison Control Center right away

Purpose:

First aid to help prevent infection in minor cuts, scrapes, and burns.

Other information

- store at controlled room temperature
- Avoid excessive heat and humidity
- Tamper Evident. Do not use if inner seal is torn, cut or open.

Ask a doctor if

Ask a doctor before use if you have deep or puncture wounds, animal bites, or serious burns.

Inactive ingredients

Hard Paraffin, Liquid Paraffin, White Soft Paraffin

Principal Display Panel

Dynarex Bacitracin Zinc Ointment:

1175 ESG.jpg